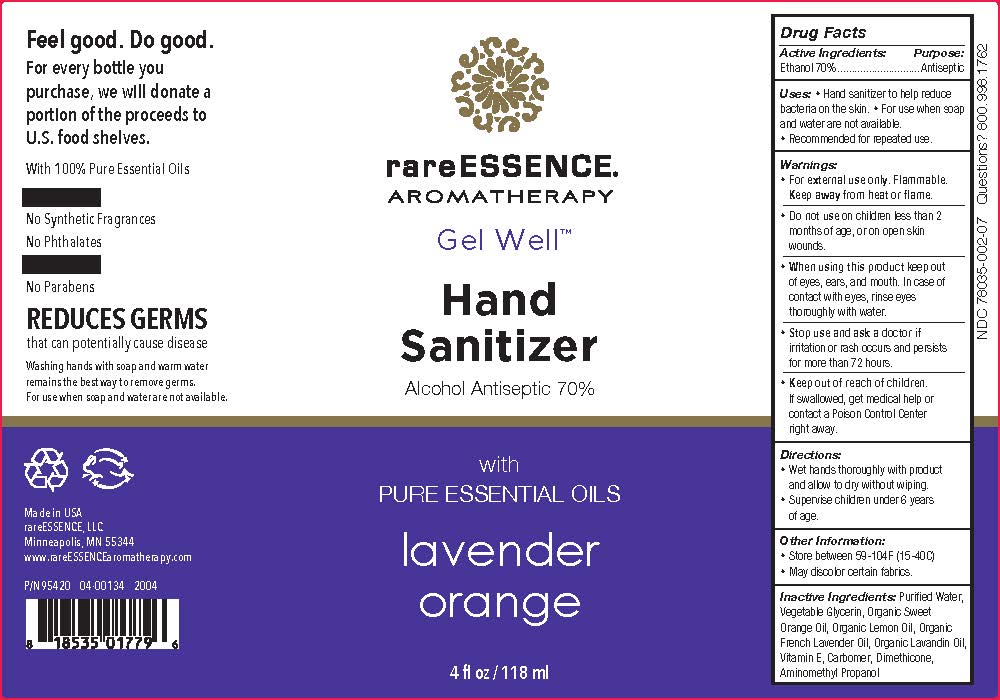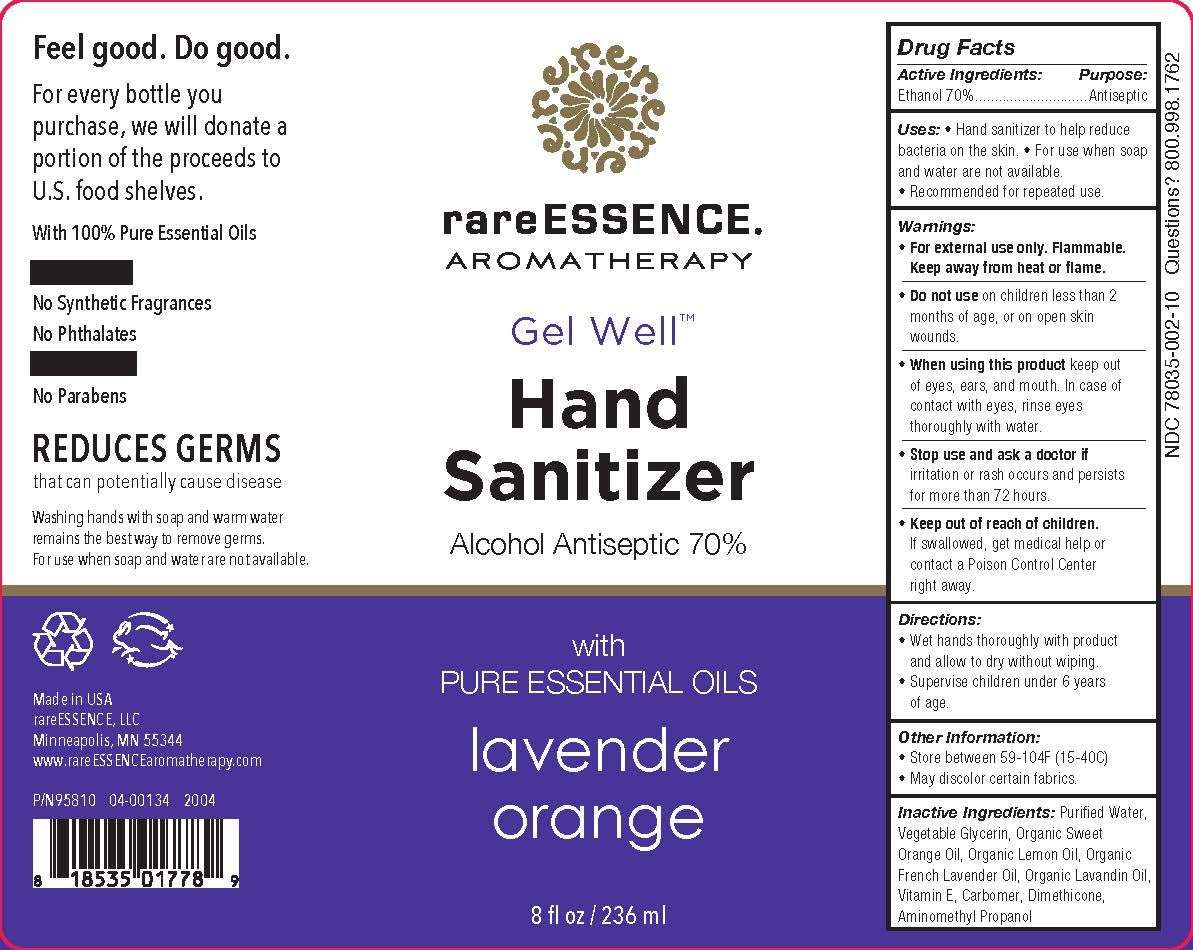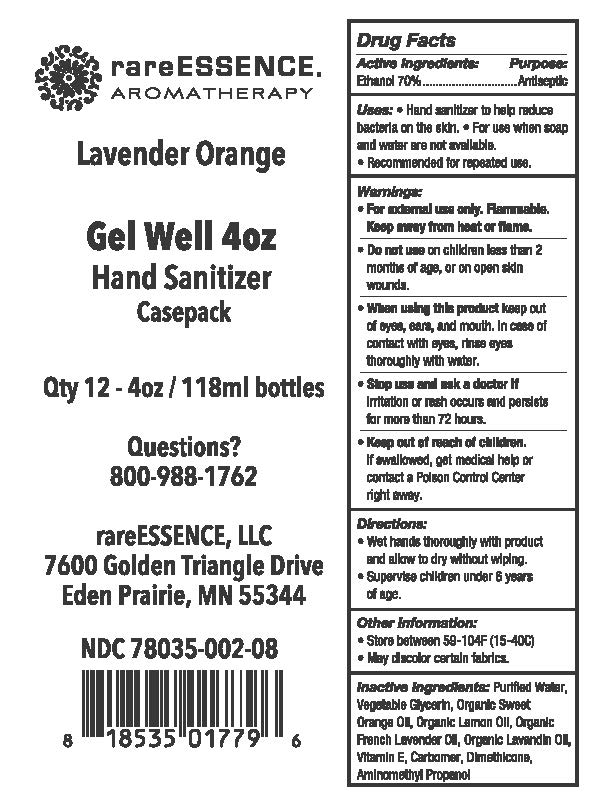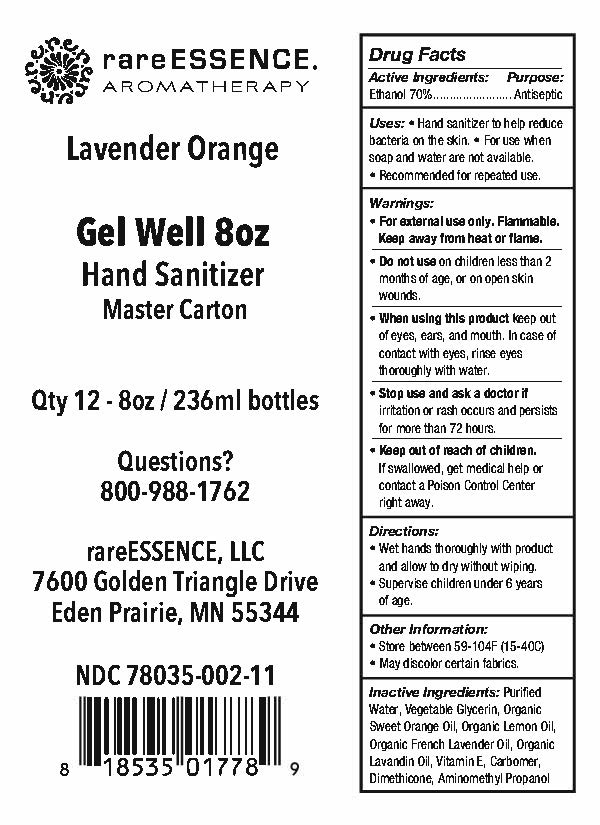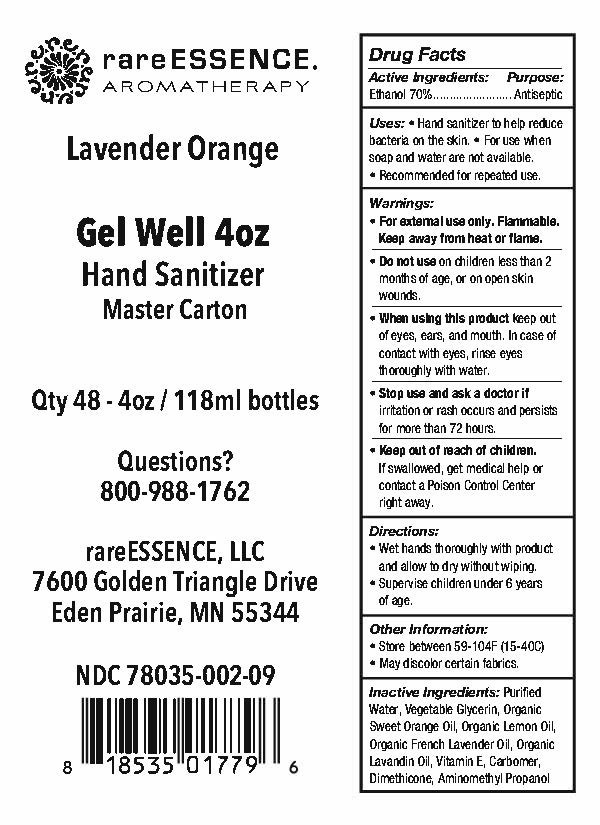 DRUG LABEL: rareEssence Gel Well Hand Sanitizer
NDC: 78035-002 | Form: GEL
Manufacturer: rareESSENCE, LLC
Category: otc | Type: HUMAN OTC DRUG LABEL
Date: 20200608

ACTIVE INGREDIENTS: ALCOHOL 70 mL/100 mL
INACTIVE INGREDIENTS: ALPHA-TOCOPHEROL; CARBOMER 940; ORANGE OIL; LAVENDER OIL; LAVANDIN OIL; WATER; LEMON OIL; GLYCERIN; DIMETHICONE 350

Drug Facts

ACTIVE INGREDIENT

Ethyl Alcohol 70%

PURPOSE

Hand and Antiseptic

INDICATIONS AND USAGE

Hand and skin antiseptic to help decrease pathogens (germs) on the skin

WARNINGS

For external use only

Flammable: Keep away from heat and flame

WHEN USING

* Avoid contact with eyes. If contact occurs flush eyes thoroughly with clean and cold water

* Do not ingest or inhale

ASK DOCTOR

* If irritation or redness develops, and/or you have open wounds or serious burns.

STOP USE

* If irritation or redness develops

* Have open wounds or serious burns

KEEP OUT OF REACH OF CHILDREN

* If swallowed get medical help or contact a Poison Control Center immediately

DOSAGE AND ADMINISTRATION

* Wet hands thourhgly with product and allow to dry without wiping

* Supervise children under 6 years of age

INACTIVE INGREDIENT

Purified water, Glycerin, Orange Oil, Lemon Oil, Lavender Oil, Lavandin Oil, Vitamin E, Carbomer, Dimethicone, Aminomethyl Propanol

Questions? 800-998-1762

PACKAGE LABEL

rareESSENCE Gel Well(TM) Hand Sanitizer

Alcohol Antiseptic 70%

with Pure Essential Oils

Lavender orange

Feel good, Do good.

For every bottle you purchase, we will donate a portion of the proceeds to U.S. food shelves

With 100% pure Essential Oils

No Synthetic Fragrances

No Phthalates

No Parabens

Reduces Germs that can potentially cause disease

Washing hands wiht souap and warm water remains the best way to remvoe germs.

For use when soap and water are not available

Made in USA

rareEssence, LLC

Minneapolis, MN 55344

www,rareESSENCEaromatherapy.com

xx oz(zzzmL) NDC 78035-002-xx